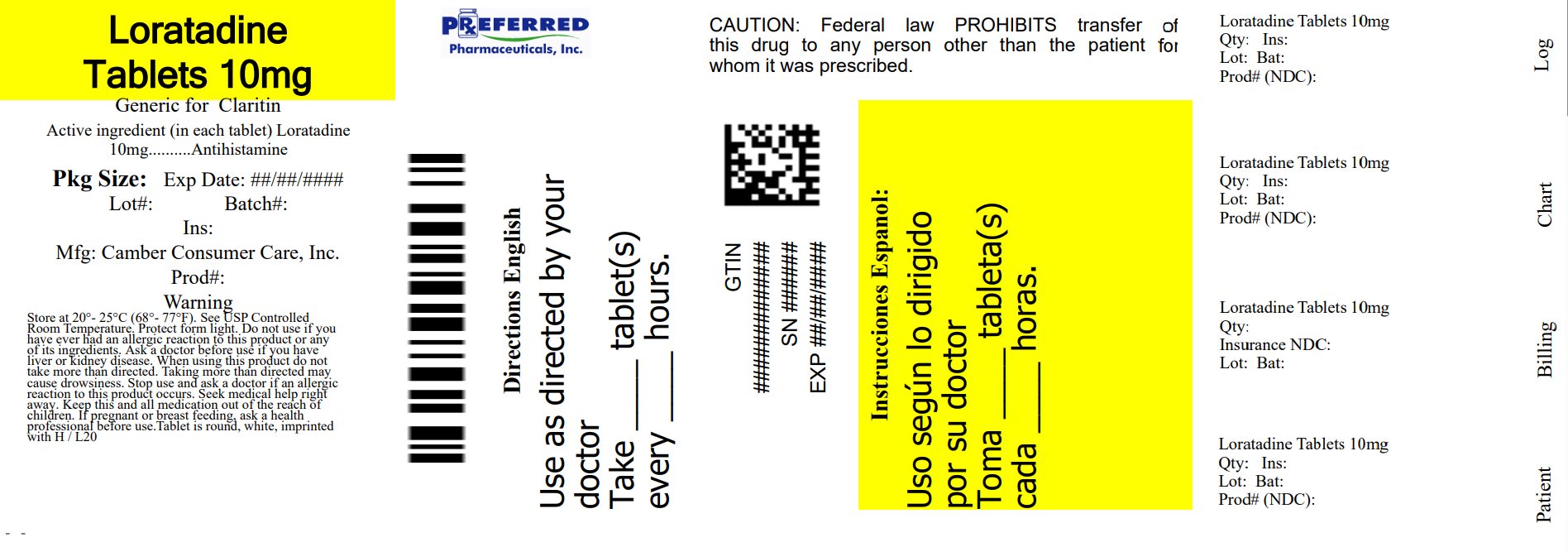 DRUG LABEL: Loratadine
NDC: 68788-8605 | Form: TABLET
Manufacturer: Preferred Pharmaceuticals Inc.
Category: otc | Type: HUMAN OTC DRUG LABEL
Date: 20250723

ACTIVE INGREDIENTS: LORATADINE 10 mg/1 1
INACTIVE INGREDIENTS: STARCH, CORN; LACTOSE MONOHYDRATE; MAGNESIUM STEARATE

Loratadine tablets USP, 10mg/antihistamine

ACTIVE INGREDIENT(S)

Active ingredient (in each tablet)
Loratadine USP, 10 mg

PURPOSE

Antihistamine

USE(S)

temporarily relieves these symptoms due to hay fever or other upper respiratory allergies:

- runny nose

- itchy, watery eyes

- sneezing

- itching of the nose or throat

DO NOT USE

if you have ever had an allergic reaction to this product or any of its ingredients.

ASK A DOCTOR BEFORE USE IF YOU HAVE

liver or kidney disease. Your doctor should determine if you need a different dose.

WHEN USING THIS PRODUCT

do not take more than directed. Taking more than directed may cause drowsiness.

STOP USE AND ASK DOCTOR IF

an allergic reaction to this product occurs. Seek medical help right away.

PREGNANCY/BREASTFEEDING

ask a health professional before use.

KEEP OUT OF REACH OF CHILDREN

In case of overdose, get medical help or contact a Poison Control Center right away.

DIRECTIONS

adults and children 6 years and over | 1 tablet daily; not more than 1 tablet in 24 hours
children under 6 years of age | ask a doctor
consumers with liver or kidney disease | ask a doctor

OTHER INFORMATION

Bottles:

- Tamper-evident: do not use if foil seal under cap, printed with "SEALED for YOUR PROTECTION" is missing, open or broken
- store between 20° to 25°C (68° to 77°F)

Blisters packs:

- safety sealed: do not use if the individual blister unit imprinted with loratadine is open or torn
- store between 20° to 25°C (68° to 77°F)
- protect from excessive moisture

INACTIVE INGREDIENTS

corn starch, lactose monohydrate, magnesium stearate, pregelatinized starch

Repackaged By: Preferred Pharmaceuticals Inc.

QUESTIONS OR COMMENTS?

Call 1-888-588-1418

PRINCIPAL DISPLAY PANEL

Loratadine-tablets-USP-10mg-30's-carton